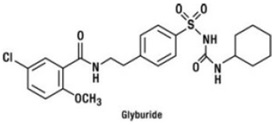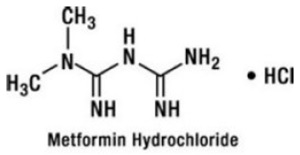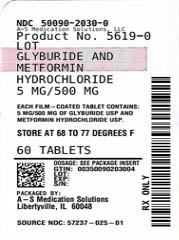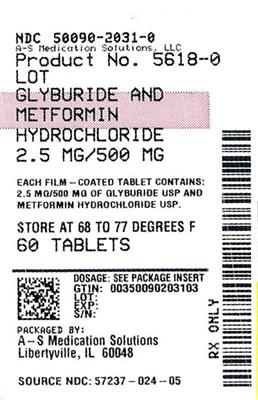 DRUG LABEL: Glyburide and Metformin Hydrochloride
NDC: 50090-2030 | Form: TABLET, FILM COATED
Manufacturer: A-S Medication Solutions
Category: prescription | Type: Human Prescription Drug Label
Date: 20260208

ACTIVE INGREDIENTS: GLYBURIDE 5 mg/1 1; METFORMIN HYDROCHLORIDE 500 mg/1 1
INACTIVE INGREDIENTS: MICROCRYSTALLINE CELLULOSE; CROSCARMELLOSE SODIUM; POVIDONE K90; MAGNESIUM STEARATE; HYPROMELLOSE 2910 (6 MPA.S); PROPYLENE GLYCOL; PEG-20 SORBITAN OLEATE; TALC; CI 77891; KI5; KI203

HIGHLIGHTS OF PRESCRIBING INFORMATION

These highlights do not include all the information needed to use GLYBURIDE AND METFORMIN HYDROCHLORIDE TABLETS safely and effectively. See full prescribing information for GLYBURIDE AND METFORMIN HYDROCHLORIDE TABLETS.
GLYBURIDE and METFORMIN HYDROCHLORIDE tablets, for oral use
Initial U.S. Approval: 2000

WARNING: LACTIC ACIDOSIS

See full prescribing information for complete boxed warning.

- Post-marketing cases of metformin-associated lactic acidosis have resulted in death, hypothermia, hypotension, and resistant bradyarrhythmias. Symptoms include malaise, myalgias, respiratory distress, somnolence, and abdominal pain. Laboratory abnormalities included elevated blood lactate levels, anion gap acidosis, increased lactate/pyruvate ratio; and metformin plasma levels generally >5 mcg/mL. (5.1)
- Risk factors include renal impairment, concomitant use of certain drugs, age ≥ 65 years old, radiological study with contrast, surgery and other procedures, hypoxic states, excessive alcohol intake, and hepatic impairment. Steps to reduce the risk of and manage metformin-associated lactic acidosis in these high risk groups are provided in the Full Prescribing Information. (5.1)
- If lactic acidosis is suspected, discontinue glyburide and metformin hydrochloride and institute general supportive measures in a hospital setting. Prompt hemodialysis is recommended. (5.1)

1 INDICATIONS AND USAGE

Glyburide and metformin hydrochloride tablets are a combination of glyburide, a sulfonylurea, and metformin hydrochloride (HCl), a biguanide, indicated as an adjunct to diet and exercise to improve glycemic control in adults with type 2 diabetes mellitus. (1)

2 DOSAGE AND ADMINISTRATION

Adult Dosage:

- Give glyburide and metformin hydrochloride tablets in divided doses, twice daily, with meals. (2.1)
- For patients not treated with either glyburide (or another sulfonylurea) or metformin HCl, initiate treatment with another formulation with a dose of 1.25 mg glyburide and 250mg metformin HCl orally, once or twice daily with meals. (2.1)
- For patients not adequately controlled on either glyburide (or another sulfonylurea) or metformin HCl alone, the recommended starting dose is 2.5 mg/500 mg or 5 mg/500 mg orally twice daily with meals. (2.1)
- For patients previously treated with a combination therapy of glyburide (or another sulfonylurea) and metformin HCl, the starting dose should not exceed the daily dose of glyburide (or equivalent dose of another sulfonylurea) and metformin HCl already being taken. (2.1)
- Increase the dose gradually on the basis of glycemic control and tolerability, up to a maximum to a maximum dose of 20 mg glyburide/2000 mg metformin HCl daily. (2.1)

Renal Impairment:

Prior to initiation, assess renal function with estimated glomerular filtration rate (eGFR) (2.4)

- Do not use in patients with eGFR below 30 mL/minute/1.73 m^2 (2.4)
- Initiation is not recommended in patients with eGFR between 30 to 45 mL/minute/1.73 m^2 (2.4)
- Assess risk/benefit if eGFR falls below 45 mL/minute/1.73 m^2 (2.4)
- Discontinue if eGFR falls below 30 mL/minute/1.73 m^2 (2.4)

Discontinuation for Iodinated Contrast Imaging Procedures:

- Glyburide and metformin hydrochloride tablets may need to be discontinued at time of, or prior to, iodinated contrast imaging procedures (2.5)

3 DOSAGE FORMS AND STRENGTHS

- Tablets: 1.25 mg glyburide and 250 mg metformin HCl (3)
- Tablets: 2.5 mg glyburide and 500 mg metformin HCl (3)
- Tablets: 5 mg glyburide and 500 mg metformin HCl (3)

4 CONTRAINDICATIONS

- Severe renal impairment (eGFR below 30 mL/min/1.73 m^2) (4, 5.1)
- Hypersensitivity to metformin or glyburide. (4)
- Acute or chronic metabolic acidosis, including diabetic ketoacidosis, with or without coma. (4)
- Concomitant administration of bosentan. (4, 7)

5 WARNINGS AND PRECAUTIONS

- Lactic Acidosis: See boxed warning. (5.1)
- Hypoglycemia: May be severe. Ensure proper patient selection, dosing, and instructions, particularly in at-risk populations (e.g., elderly, renally impaired) and when used with other anti-diabetic medications. (5.2)
- Potential Increased Risk of Cardiovascular Mortality with Sulfonylureas: Inform patient of risks, benefits and treatment alternatives. (5.3)
- Hemolytic anemia: Can occur if glucose 6-phosphate dehydrogenase (G6PD) deficient. Consider a non-sulfonylurea alternative. (5.4)
- Vitamin B12 Deficiency: Metformin may lower vitamin B12 levels. Measure hematological parameters annually and vitamin B12 at 2 to 3 year intervals and manage any abnormalities. (5.5)

6 ADVERSE REACTIONS

Most common (>5%) adverse reactions to glyburide and metformin hydrochloride diarrhea, headache, nausea/vomiting, abdominal pain, and dizziness. (6.1)

To report SUSPECTED ADVERSE REACTIONS, contact Rising Health, LLC at 1-833-395-6928 or FDA at 1-800-FDA-1088 or www.fda.gov/medwatch.

7 DRUG INTERACTIONS

- Carbonic anhydrase inhibitors may increase risk of lactic acidosis. Consider more frequent monitoring. (7)
- Drugs that reduce metformin clearance (such as ranolazine, vandetanib, dolutegravir, and cimetidine) may increase the accumulation of metformin. Consider the benefits and risks of concomitant use. (7)
- Alcohol can potentiate the effect of metformin on lactate metabolism. Warn patients against excessive alcohol intake. (7)
- The hypoglycemic action of glyburide and metformin hydrochloride may be potentiated by certain drugs. (7)
- Concomitant administration of colesevalam may led to reduced glyburide absorption. (7)

8 USE IN SPECIFIC POPULATIONS

- Pregnancy: Glyburide and metformin hydrochloride should be discontinued at least two weeks before expected delivery. (8.1)
- Females and Males of Reproductive Potential: Advise premenopausal females of the potential for an unintended pregnancy. (8.3)
- Geriatric Use: Assess renal function more frequently. (8.5)
- Hepatic Impairment: Avoid use in patients with hepatic impairment. (8.7)

FULL PRESCRIBING INFORMATION

WARNING: LACTIC ACIDOSIS

Postmarketing cases of metformin-associated lactic acidosis have resulted in death, hypothermia, hypotension, and resistant bradyarrhythmias. The onset of metforminassociated lactic acidosis is often subtle, accompanied only by nonspecific symptoms such as malaise, myalgias, respiratory distress, somnolence, and abdominal pain. Metformin-associated lactic acidosis was characterized by elevated blood lactate levels (>5 mmol/Liter), anion gap acidosis (without evidence of ketonuria or ketonemia), an increased lactate/pyruvate ratio; and metformin plasma levels generally >5 mcg/mL [see Warnings and Precautions (5.1)].

Risk factors for metformin-associated lactic acidosis include renal impairment, concomitant use of certain drugs (e.g., carbonic anhydrase inhibitors such as topiramate), age 65 years old or greater, having a radiological study with contrast, surgery and other procedures, hypoxic states (e.g., acute congestive heart failure), excessive alcohol intake, and hepatic impairment.

Steps to reduce the risk of and manage metformin-associated lactic acidosis in these high risk groups are provided [see Dosage and Administration (2.3), Contraindications (4) and Warnings and Precautions (5.1)].

If metformin-associated lactic acidosis is suspected, immediately discontinue glyburide and metformin hydrochloride and institute general supportive measures in a hospital setting. Prompt hemodialysis is recommended [see Warnings and Precautions (5.1)].

1 INDICATIONS AND USAGE

Glyburide and metformin hydrochloride tablets are indicated as an adjunct to diet and exercise to improve glycemic control in adults with type 2 diabetes mellitus.

2 DOSAGE AND ADMINISTRATION

2.1 Dosage

- Give glyburide and metformin hydrochloride tablets in divided doses, twice daily, with meals.
- For patients not treated with either glyburide (or another sulfonylurea) or metformin hydrochloride (HCl), initiate treatment with another formulation of glyburide and metformin HCl at a starting dose of 1.25 mg glyburide and 250mg metformin HCl orally, once or twice daily with meals.
- For patients not adequately controlled on either glyburide (or another sulfonylurea) or metformin HCl alone, the recommended starting dose of glyburide and metformin hydrochloride tablets is 2.5 mg/500 mg or 5 mg/500 mg orally twice daily with meals.
- For patients previously treated with a combination therapy of glyburide (or another sulfonylurea) and metformin HCl, the starting dose of glyburide and metformin hydrochloride tablets should not exceed the daily dose of glyburide (or equivalent dose of another sulfonylurea) and metformin HCl already being taken.
- Increase the dose gradually on the basis of glycemic control and tolerability, up to a maximum to a maximum dose of 20 mg glyburide/2000 mg metformin HCl daily.

2.2 Patients Receiving Colesevelam

- Administer glyburide and metformin hydrochloride tablets at least 4 hours prior to colesevelam for patients taking both drugs concomitantly [see Drug Interactions (7)].

2.3 Recommendations for Use in Renal Impairment

- Assess renal function prior to initiation of glyburide and metformin hydrochloride tablets and periodically thereafter.
- Glyburide and metformin hydrochloride tablets are contraindicated in patients with an estimated glomerular filtration rate (eGFR) below 30 mL/minute/1.73 m^2.
- Initiation of glyburide and metformin hydrochloride tablets in patients with an eGFR between 30 to 45 mL/minute/1.73 m^2 is not recommended.
- In patients taking glyburide and metformin hydrochloride tablets whose eGFR later falls below 45 mL/min/1.73 m^2, assess the benefit risk of continuing therapy.
- Discontinue glyburide and metformin hydrochloride tablets if the patient’s eGFR later falls below 30 mL/minute/1.73 m^2 [see Warnings and Precautions (5.1)].

2.4 Discontinuation for Iodinated Contrast Imaging Procedures

- Discontinue glyburide and metformin hydrochloride tablets at the time of, or prior to, an iodinated contrast imaging procedure in patients with an eGFR between 30 and 60 mL/min/1.73 m^2; in patients with a history of liver disease, alcoholism or heart failure; or in patients who will be administered intra-arterial iodinated contrast.
- Re-evaluate eGFR 48 hours after the imaging procedure; restart glyburide and metformin hydrochloride tablets if renal function is stable.

3 DOSAGE FORMS AND STRENGTHS

Glyburide and metformin hydrochloride tablets, USP are available as:

- 1.25 mg/250 mg Tablets: Yellow, capsule shaped, biconvex, film-coated tablet with ‘A’ debossed on one side and ‘46’ on the other side.
- 2.5 mg/500 mg Tablets: Light pink, capsule shaped, biconvex, film-coated tablet with ‘A’ debossed on one side and ‘47’ on the other side.
- 5 mg/500 mg Tablets: Yellow, capsule shaped, biconvex, film-coated tablet with ‘A’ debossed on one side and ‘48’ on the other side

4 CONTRAINDICATIONS

Glyburide and metformin hydrochloride tablets are contraindicated in patients with:

- Severe renal impairment (eGFR below 30 mL/min/1.73 m^2) [see Warnings and Precautions (5.1)].
- Hypersensitivity to metformin or glyburide.
- Acute or chronic metabolic acidosis, including diabetic ketoacidosis, with or without coma.
- Concomitant administration of bosentan [see Drug Interactions (7)].

5 WARNINGS AND PRECAUTIONS

5.1 Lactic Acidosis

There have been postmarketing cases of metformin-associated lactic acidosis, including fatal cases. These cases had a subtle onset and were accompanied by nonspecific symptoms such as malaise, myalgias, abdominal pain, respiratory distress, or increased somnolence; however, hypotension and resistant bradyarrhythmias have occurred with severe acidosis. Metformin-associated lactic acidosis was characterized by elevated blood lactate concentrations (>5 mmol/L), anion gap acidosis (without evidence of ketonuria or ketonemia), and an increased lactate: pyruvate ratio; metformin plasma levels were generally >5 mcg/mL. Metformin decreases liver uptake of lactate increasing lactate blood levels which may increase the risk of lactic acidosis, especially in patients at risk.

If metformin-associated lactic acidosis is suspected, general supportive measures should be instituted promptly in a hospital setting, along with immediate discontinuation of glyburide and metformin hydrochloride. In glyburide and metformin hydrochloride treated patients with a diagnosis or strong suspicion of lactic acidosis, prompt hemodialysis is recommended to correct the acidosis and remove accumulated metformin (metformin HCl is dialyzable with a clearance of up to 170 mL/min under good hemodynamic conditions). Hemodialysis has often resulted in reversal of symptoms and recovery.

Educate patients and their families about the symptoms of lactic acidosis and, if these symptoms occur, instruct them to discontinue glyburide and metformin hydrochloride and report these symptoms to their healthcare provider.

For each of the known and possible risk factors for metformin-associated lactic acidosis, recommendations to reduce the risk of and manage metformin-associated lactic acidosis are provided below:

- Renal Impairment—The postmarketing metformin-associated lactic acidosis cases primarily occurred in patients with significant renal impairment.

The risk of metformin accumulation and metformin-associated lactic acidosis increases with the severity of renal impairment because metformin is substantially excreted by the kidney. Clinical recommendations based upon the patient’s renal function include [see Dosage and Administration (2.1), Clinical Pharmacology (12.3)]:

-
  - Before initiating glyburide and metformin hydrochloride, obtain an estimated glomerular filtration rate (eGFR).
  - Glyburide and metformin hydrochloride is contraindicated in patients with an eGFR less than 30 mL/min/1.73 m^2 [see CONTRAINDICATIONS (4)].
  - Initiation of glyburide and metformin hydrochloride is not recommended in patients with eGFR between 30 to 45 mL/min/1.73 m^2.
  - Obtain an eGFR at least annually in all patient taking glyburide and metformin hydrochloride. In patients at risk for the development of renal impairment (e.g., the elderly), renal function should be assessed more frequently.
  - In patients taking glyburide and metformin hydrochloride whose eGFR falls below 45 mL/min/1.73 m^2, assess the benefit and risk of continuing therapy.
  - Drug interactions—The concomitant use of glyburide and metformin hydrochloride with specific drugs may increase the risk of metformin-associated lactic acidosis: those that impair renal function, result in significant hemodynamic change, interfere with acid-base balance, or increase metformin accumulation [see Drug Interactions (7)]. Consider more frequent monitoring of patients.
  - Age 65 or Greater—The risk of metformin-associated lactic acidosis increases with the patient’s age because elderly patients have a greater likelihood of having hepatic, renal, or cardiac impairment than younger patients. Assess renal function more frequently in elderly patients.
  - Radiologic studies with contrast—Administration of intravascular iodinated contrast agents in metformin-treated patients has led to an acute decrease in renal function and the occurrence of lactic acidosis. Stop glyburide and metformin hydrochloride at the time of, or prior to, an iodinated contrast imaging procedure in patients with an eGFR between 30 and 60 mL/min/1.73 m^2; in patients with a history of hepatic impairment, alcoholism or heart failure, or in patients who will be administered intra-arterial iodinated contrast. Reevaluate eGFR 48 hours after the imaging procedure, and restart glyburide and metformin hydrochloride if renal function is stable.
  - Surgery and other procedures—Withholding of food and fluids during surgical or other procedures may increase the risk for volume depletion, hypotension, and renal impairment. Glyburide and metformin hydrochloride should be temporarily discontinued while patients have restricted food and fluid intake.
  - Hypoxic states—Several of the postmarketing cases of metformin-associated lactic acidosis occurred in the setting of acute congestive heart failure (particularly when accompanied by hypoperfusion and hypoxemia). Cardiovascular collapse (shock), acute myocardial infarction, sepsis, and other conditions associated with hypoxemia have been associated with lactic acidosis and may cause prerenal azotemia. When such an event occurs, discontinue glyburide and metformin hydrochloride.
  - Excessive Alcohol intake—Alcohol potentiates the effect of metformin on lactate metabolism. Patients should be warned against excessive alcohol intake, acute or chronic, while receiving glyburide and metformin hydrochloride.
  - Hepatic impairment—Patients with hepatic impairment have developed cases of metformin-associated lactic acidosis. This may be due to impaired lactate clearance resulting in higher lactate blood levels. Therefore, avoid use of glyburide and metformin hydrochloride in patients with clinical or laboratory evidence of hepatic disease.

5.2 Hypoglycemia

All sulfonylurea drugs, including glyburide and metformin hydrochloride, are capable of producing severe hypoglycemia [see Adverse Reactions (6)]. Concomitant use of glyburide and metformin hydrochloride with other anti-diabetic medication can increase the risk of hypoglycemia. A lower dose of glyburide and metformin hydrochloride may be required to minimize the risk of hypoglycemia when combining it with other anti-diabetic medications.

Educate patients to recognize and manage hypoglycemia. When initiating and increasing glyburide and metformin hydrochloride in patients who may be predisposed to hypoglycemia (e.g., the elderly, patients with renal impairment, patients on other anti-diabetic medications) start with a lower dose. Debilitated or malnourished patients, and those with adrenal, pituitary, or hepatic impairment are particularly susceptible to the hypoglycemic action of anti-diabetic medications. Hypoglycemia is also more likely to occur when caloric intake is deficient, after severe or prolonged exercise, or when alcohol is ingested.

The patient’s ability to concentrate and react may be impaired as a result of hypoglycemia. Early warning symptoms of hypoglycemia may be different or less pronounced in patients with autonomic neuropathy, the elderly, and in patients who are taking beta-adrenergic blocking medications or other sympatholytic agents. These situations may result in severe hypoglycemia before the patient is aware of the hypoglycemia.

These impairments may present a risk in situations where these abilities are especially important, such as driving or operating other machinery. Severe hypoglycemia can lead to unconsciousness or convulsions and may result in temporary or permanent impairment of brain function or death.

5.3 Cardiovascular Mortality

The administration of oral hypoglycemic drugs has been reported to be associated with increased cardiovascular mortality as compared to treatment with diet alone or diet plus insulin. This warning is based on the study conducted by the University Group Diabetes Program (UGDP), a long-term prospective clinical study designed to evaluate the effectiveness of glucose-lowering drugs in preventing or delaying vascular complications in patients with type 2 diabetes mellitus. The study involved 823 patients who were randomly assigned to 1 of 4 treatment groups.

UGDP reported that patients treated for 5 to 8 years with diet plus a fixed dose of tolbutamide (1.5 grams per day) had a rate of cardiovascular mortality approximately 2½ times that of patients treated with diet alone. A significant increase in total mortality was not observed, but the use of tolbutamide was discontinued based on the increase in cardiovascular mortality, thus limiting the opportunity for the study to show an increase in overall mortality. Despite controversy regarding the interpretation of these results, the findings of the UGDP study provide an adequate basis for this warning. The patient should be informed of the potential risks and benefits of glyburide and of alternative modes of therapy.

Although only one drug in the sulfonylurea class (tolbutamide) was included in this study, it is prudent from a safety standpoint to consider that this warning may also apply to other hypoglycemic drugs in this class, in view of their close similarities in mode of action and chemical structure.

5.4 Hemolytic Anemia

Treatment of patients with glucose-6-phosphate dehydrogenase (G6PD) deficiency with sulfonylurea agents, including glyburide and metformin hydrochloride, can lead to hemolytic anemia. Avoid use of glyburide and metformin hydrochloride in patients with G6PD deficiency. In postmarketing reports, hemolytic anemia has also been reported in patients who did not have known G6PD deficiency.

5.5 Vitamin B12 Deficiency

In clinical studies of 29-week duration with metformin HCl tablets, a decrease to subnormal levels of previously normal serum vitamin B12 levels, was observed in approximately 7% of patients. Such decrease, possibly due to interference with B12 absorption from the B12-intrinsic factor complex, may be associated with anemia but appears to be rapidly reversible with discontinuation of metformin or vitamin B12 supplementation. Certain individuals (those with inadequate vitamin B12 or calcium intake or absorption) appear to be predisposed to developing subnormal vitamin B12 levels. Measure hematologic parameters on an annual basis and vitamin B12 at 2 to 3 year intervals in patients on glyburide and metformin hydrochloride and manage any abnormalities [see Adverse Reactions (6.1)].

5.6 Macrovascular Outcomes

There have been no clinical studies establishing conclusive evidence of macrovascular risk reduction with glyburide and metformin hydrochloride.

6 ADVERSE REACTIONS

The following adverse reactions are also discussed elsewhere in the labeling:

- Lactic Acidosis [see Boxed Warning and Warnings and Precautions (5.1)]
- Hypoglycemia [see Warnings and Precautions (5.2)]
- Cardiovascular mortality [see Warnings and Precautions (5.3)]
- Hemolytic anemia [see Warnings and Precautions (5.4)]
- Vitamin B12 Deficiency [see Warnings and Precautions (5.5)]

6.1 Clinical Studies Experience

Because clinical studies are conducted under widely varying conditions, adverse reaction rates observed in the clinical studies of a drug cannot be directly compared to rates in the clinical studies of another drug and may not reflect the rates observed in practice.

In double-blind clinical studies with glyburide and metformin hydrochloride as initial therapy or as second-line therapy of 20 and 14 weeks, respectively (see section 14), a total of 642 patients received glyburide and metformin hydrochloride, 312 received metformin HCl, 324 received glyburide, and 161 received placebo. Adverse reactions are listed in Table 1.

Table 1: Adverse Reactions Occurring >5% in Double-Blind Clinical Studies of Glyburide And Metformin Hydrochloride Used as Initial (20 Weeks) or Second-Line (14 Weeks) Therapy
Adverse Reaction | Number (%) of Patients
Adverse Reaction | Placebo N=161 | Glyburide N=324 | Metformin HCl N=312 | Glyburide and Metformin Hydrochloride N=642
Diarrhea | 6% | 6% | 21% | 17%
Headache | 11% | 11% | 9% | 9%
Nausea/vomiting | 6% | 5% | 12% | 8%
Abdominal pain | 4% | 3% | 8% | 7%
Dizziness | 4% | 6% | 4% | 6%

Hypoglycemia

The incidence of reported symptoms of hypoglycemia (such as dizziness, shakiness, sweating, and hunger), in the initial therapy study of glyburide and metformin hydrochloride are summarized in Table 2. For patients with a baseline HbA1c between 8% and 11% treated with glyburide and metformin hydrochloride 2.5 mg/500 mg as initial therapy, the frequency of hypoglycemic symptoms was 30% to 35%. As second-line therapy in patients inadequately controlled on sulfonylurea alone, approximately 6.8% of all patients treated with glyburide and metformin hydrochloride experienced hypoglycemic symptoms.

Gastrointestinal Reactions

The incidence of gastrointestinal (GI) side effects (diarrhea, nausea/vomiting, and abdominal pain) in the glyburide and metformin hydrochloride initial therapy study are summarized in Table 2. Across all glyburide and metformin hydrochloride studies, GI symptoms were the most common adverse events with glyburide and metformin hydrochloride and were more frequent at higher dose levels. In controlled studies, <2% of patients discontinued glyburide and metformin hydrochloride therapy due to GI adverse events.

Table 2: Hypoglycemia or Gastrointestinal Adverse Reactions in a Placebo- and Active-Controlled Study of Glyburide and Metformin Hydrochloride as Initial Therapy (20 Weeks)
Variable | Placebo N=161 | Glyburide Tablets N=160 | Metformin HCl Tablets N=159 | Glyburide and Metformin Hydrochloride 1.25 mg/250 mg Tablets N=158 | Glyburide and Metformin Hydrochloride 2.5 mg/500 mg Tablets N=162
Number (%) of patients with symptoms of hypoglycemia | 3% | 21% | 3% | 11% | 38%
Number (%) of patients with gastrointestinal adverse events | 24% | 24% | 43% | 32% | 38%

Dermatologic Reactions

Allergic skin reactions, e.g., pruritus, erythema, urticaria, and morbilliform or maculopapular eruptions, occur in 1.5% of glyburide-treated patients. These may be transient and may disappear despite continued use.

6.2 Postmarketing Adverse Reactions

The following adverse reactions have been identified during post-approval use of glyburide and metformin hydrochloride. Because these reactions are reported voluntarily from a population of uncertain size, it is not always possible to reliably estimate their frequency or establish a causal relationship to drug exposure.

Allergic: Angioedema, arthralgia, myalgia, and vasculitis have been reported.

Dermatologic: Porphyria cutanea tarda and photosensitivity reactions have been reported with sulfonylureas.

Hematologic: Leukopenia, agranulocytosis, thrombocytopenia, which occasionally may present as purpura, hemolytic anemia, aplastic anemia, and pancytopenia, have been reported with sulfonylureas.

Hepatic: Cholestatic, hepatocellular, and mixed hepatocellular liver injury have been reported with postmarketing use of metformin. Cholestatic jaundice and hepatitis may occur rarely with glyburide, which may progress to liver failure. Liver function abnormalities, including isolated transaminase elevations, have been reported.

Metabolic: Hepatic porphyria reactions have been reported with sulfonylureas; however, these have not been reported with glyburide. Disulfiram-like reactions have been reported very rarely with glyburide. Cases of hyponatremia have been reported with glyburide and all other sulfonylureas, most often in patients who are on other medications or have medical conditions known to cause hyponatremia or increase release of antidiuretic hormone.

Other Reactions: Changes in accommodation and/or blurred vision have been reported with glyburide and other sulfonylureas. These are thought to be related to fluctuation in glucose levels.

7 DRUG INTERACTIONS

Table 3 presents clinically significant drug interactions with glyburide and metformin hydrochloride.

Table 3: Clinically Significant Drug Interactions with Glyburide and Metformin Hydrochloride

Carbonic Anhydrase Inhibitors
Clinical Impact: | Carbonic anhydrase inhibitors frequently cause a decrease in serum bicarbonate and induce non-anion gap, hyperchloremic metabolic acidosis. Concomitant use of these drugs with glyburide and metformin hydrochloride may increase the risk for lactic acidosis.
Intervention: | Consider more frequent monitoring of these patients.
Examples: | Topiramate, zonisamide, acetazolamide and dichlorphenamide.
Drugs that Reduce Metformin Clearance
Clinical Impact: | Concomitant use of drugs that interfere with common renal tubular transport systems involved in the renal elimination of metformin (e.g., organic cationic transporter-2 [OCT2] / multidrug and toxin extrusion [MATE] inhibitors) could increase systemic exposure to metformin and may increase the risk for lactic acidosis [see Clinical Pharmacology (12.3)].
Intervention: | Consider the benefits and risks of concomitant use with glyburide and metformin hydrochloride.
Examples: | Ranolazine, vandetanib, dolutegravir, and cimetidine.
Alcohol
Clinical Impact: | Alcohol is known to potentiate the effect of metformin on lactate metabolism.
Intervention: | Warn patients against excessive alcohol intake while receiving glyburide and metformin hydrochloride.
Drugs that potentiate the hypoglycemic action of glyburide and metformin hydrochloride
Clinical Impact: | Certain drugs may potentiate the hypoglycemic action of sulfonylureas, one of the components of glyburide and metformin hydrochloride.
Intervention: | Closely observe patient for hypoglycemia during co-administration and for loss of glycemic control when withdrawing these agents.
Examples: | Nonsteroidal anti-inflammatory agents and other highly protein-boind drugs, salicylcates, sulfonamides, chloramphenicol, probenecid, coumarins, monoamine oxidase inhibitors, beta-adrenergic blocking agents; potentially with ciprofloxacin, micronazole.
Bosentan
Clinical Impact: | Increased risk of liver enzyme elevations was observed.
Intervention: | Concomitant administration is contraindicated.
Colesevalam
Clinical Impact: | Concomitant administration may led to reduced glyburide absorption (AUC and Cmax: -32% and -47%, respectively).
Intervention: | Glyburide and metformin hydrochloride should be administered at least 4 hours prior to colesevelam.
Drugs Reducing Glycemic Control
Clinical Impact: | Certain drugs tend to produce hyperglycemia and may lead to loss of glycemic control.
Intervention: | When such drugs are administered to a patient receiving glyburide and metformin hydrochloride observe the patient closely for loss of blood glucose control. When such drugs are withdrawn from a patient receiving glyburide and metformin hydrochloride, observe the patient closely for hypoglycemia.
Examples: | Thiazides and other diuretics, corticosteroids, phenothiazines, thyroid products, estrogens, oral contraceptives, phenytoin, nicotinic acid, sympathomimetics, calcium channel blockers, and isoniazid.

8 USE IN SPECIFIC POPULATIONS

8.1 Pregnancy

Risk Summary

Available data from a small number of published studies and postmarketing experience with glyburide use in pregnancy over decades have not identified any drug associated risks for major birth defects, miscarriage, or adverse maternal outcomes. However, sulfonylureas (including glyburide) cross the placenta and have been associated with neonatal adverse reactions such as hypoglycemia. Therefore, glyburide and metformin hydrochloride should be discontinued at least two weeks before expected delivery [see Clinical Considerations]. Limited data with metformin in pregnant women are not sufficient to determine a drug-associated risk for major birth defects or miscarriage. Published studies with metformin use during pregnancy have not reported a clear association with metformin and major birth defect or miscarriage risk [see Data]. There are risks to the mother and fetus associated with poorly controlled diabetes mellitus in pregnancy [see Clinical Considerations].

No evidence of harm to the fetus was observed when doses up to 500 times the maximum recommended human dose of 20 mg of glyburide, based on body surface area, were administered to rats and rabbits in reproduction studies.

No adverse developmental effects were observed when metformin was administered to pregnant Sprague Dawley rats and rabbits during the period of organogenesis at doses up to 3- and 6- times, respectively, a 2000 mg clinical dose, based on body surface area [see Data].

The estimated background risk of major birth defects is 6 to 10% in women with pre-gestational diabetes mellitus with an HbA1c >7 and has been reported to be as high as 20 to 25% in women with a HbA1c >10. The estimated background risk of miscarriage for the indicated population is unknown. In the U.S. general population, the estimated background risk of major birth defects and miscarriage in clinically recognized pregnancies is 2 to 4% and 15 to 20%, respectively.

Clinical Considerations

Disease-associated maternal and/or embryo/fetal risk

Poorly controlled diabetes mellitus in pregnancy increases the maternal risk for diabetic ketoacidosis, pre-eclampsia, spontaneous abortions, preterm delivery, and delivery complications. Poorly controlled diabetes mellitus increases the fetal risk for major birth defects, stillbirth, and macrosomia related morbidity.

Fetal/Neonatal Adverse Reactions

Neonates of women with gestational diabetes who are treated with sulfonylureas during pregnancy may be at increased risk for neonatal intensive care admission and may develop respiratory distress, hypoglycemia, birth injury, and be large for gestational age. Prolonged severe hypoglycemia, lasting 4 to 10 days, has been reported in neonates born to mothers receiving a sulfonylurea at the time of delivery and has been reported with the use of agents with a prolonged half-life. Observe newborns for symptoms of hypoglycemia and respiratory distress and manage accordingly.

Dose adjustments during pregnancy and the postpartum period

Due to reports of prolonged severe hypoglycemia in neonates born to mothers receiving a sulfonylurea at the time of delivery, glyburide and metformin hydrochloride should be discontinued at least two weeks before expected delivery [see Fetal/Neonatal Adverse Reactions].

Data

Human Data

Published data from post-marketing studies have not reported a clear association with metformin and major birth defects, miscarriage, or adverse maternal or fetal outcomes when metformin was used during pregnancy. However, these studies cannot definitely establish the absence of any metformin-associated risk because of methodological limitations, including small sample size and inconsistent comparator groups.

Animal Data

Reproduction studies were performed in rats and rabbits at doses up to 500 times the maximum recommended human dose of 20 mg of glyburide based on body surface area comparisons and revealed no evidence of harm to the fetus.

Metformin did not adversely affect development outcomes when administered to pregnant rats and rabbits at doses up to 600 mg/kg/day. This represents an exposure of about 3 and 6 times a 2000 mg clinical dose based on body surface area comparisons for rats and rabbits, respectively. Determination of fetal concentrations demonstrated a partial placental barrier to metformin.

8.2 Lactation

Risk Summary

Breastfed infants of lactating women using glyburide and metformin hydrochloride should be monitored for symptoms of hypoglycemia [see Clinical Considerations]. Although glyburide was negligible in human milk in one small clinical lactation study; this result is not conclusive because of the limitations of the assay used in the study. There are no data on the effects of glyburide on milk production. Limited published studies report that metformin is present in human milk [see Data]. However, there is insufficient information to determine the effects of metformin on the breastfed infant and no available information on the effects of metformin on milk production. Therefore, the developmental and health benefits of breastfeeding should be considered along with the mother’s clinical need for glyburide and metformin hydrochloride and any potential adverse effects on the breastfed child from glyburide and metformin hydrochloride or from the underlying maternal condition.

Clinical Considerations

Monitoring for adverse reactions

Monitor breastfed infants for signs of hypoglycemia (e.g., jitters, cyanosis, apnea, hypothermia, excessive sleepiness, poor feeding, seizures).

Data

Published clinical lactation studies report that metformin is present in human milk which resulted in infant doses approximately 0.11% to 1% of the maternal weight-adjusted dosage and a milk/plasma ratio ranging between 0.13 and 1. However, the studies were not designed to definitely establish the risk of use of metformin during lactation because of small sample size and limited adverse event data collected in infants.

8.3 Females and Males of Reproductive Potential

Discuss the potential for unintended pregnancy with premenopausal women as therapy with glyburide and metformin hydrochloride may result in ovulation in some anovulatory women.

8.4 Pediatric Use

Safety and effectiveness of glyburide and metformin hydrochloride have not been established in pediatric patients.

8.5 Geriatric Use

Of the 642 patients who received glyburide and metformin hydrochloride in double-blind clinical studies, 23.8% were 65 and older while 2.8% were 75 and older. No overall differences in effectiveness or safety were observed between these patients and younger patients, but greater sensitivity of some older individuals cannot be ruled out. Elderly patients are particularly susceptible to the hypoglycemic action of anti-diabetic agents. Hypoglycemia may be difficult to recognize in these patients.

In general, dose selection for an elderly patient should be cautious, usually starting at the low end of the dosing range, reflecting the greater frequency of decreased hepatic, renal, or cardiac function, and of concomitant disease or other drug therapy and the higher risk of hypoglycemia and lactic acidosis. Assess renal function more frequently in elderly patients [see Dosage and Administration (2) and Warnings and Precautions (5.1)].

8.6 Renal Impairment

Metformin is substantially excreted by the kidney, and the risk of metformin accumulation and lactic acidosis increases with the degree of renal impairment. Glyburide and metformin hydrochloride is contraindicated in severe renal impairment, patients with an estimated glomerular filtration rate (eGFR) below 30 mL/min/1.73 m^2 [see Dosage and Administration (2.3), Contraindications (4), Warnings and Precautions (5.1), and Clinical Pharmacology (12.3)].

8.7 Hepatic Impairment

Use of metformin in patients with hepatic impairment has been associated with some cases of lactic acidosis. Glyburide and metformin hydrochloride is not recommended in patients with hepatic impairment [see Warnings and Precautions (5.1)].

10 OVERDOSAGE

Glyburide

Overdosage of sulfonylureas, including glyburide tablets, can produce hypoglycemia. Mild hypoglycemic symptoms, without loss of consciousness or neurological findings, should be treated with oral glucose. Severe hypoglycemic reactions with coma, seizure, or other neurological impairment are medical emergencies requiring immediate treatment. The patient should be treated with glucagon or intravenous glucose. Patients should be closely monitored for a minimum of 24 to 48 hours since hypoglycemia may recur after apparent clinical recovery. Clearance of glyburide from plasma may be prolonged in persons with liver disease. Because of the extensive protein binding of glyburide, dialysis is unlikely to be of benefit.

Metformin

Overdose of metformin has occurred, including ingestion of amounts greater than 50 g. Hypoglycemia was reported in approximately 10% of cases, but no causal association with metformin has been established. Lactic acidosis has been reported in approximately 32% of metformin overdose cases [see Warnings and Precautions (5.1)]. Metformin is dialyzable with a clearance of up to 170 mL/min under good hemodynamic conditions. Therefore, hemodialysis may be useful for removal of accumulated drug from patients in whom metformin overdosage is suspected.

11 DESCRIPTION

Glyburide and metformin hydrochloride tablets, USP for oral use contain glyburide USP and metformin hydrochloride USP.

Glyburide USP is a sulfonylurea and its chemical name is 1-[[p-[2-(5-chloro-o-anisamido) ethyl]phenyl]sulfonyl]-3-cyclo-hexylurea. Glyburide USP is a white to off-white crystalline compound with molecular formula of C23H28ClN3O5S and a molecular weight of 494.01. The structural formula is represented below.

Metformin hydrochloride USP is a biguanide in hydrochloride salt form and its chemical name is N,N-dimethylimidodicarbonimidic diamide monohydrochloride. It is a white to off-white crystalline compound with molecular formula of C4H12ClN5 (monohydrochloride) and a molecular weight of 165.63. Metformin is freely soluble in water and is practically insoluble in acetone, ether, and chloroform. The pKa of metformin is 12.4. The pH of a 1% aqueous solution of metformin is 6.68. The structural formula is as shown:

Glyburide and metformin hydrochloride tablets, USP are available in film-coated containing 1.25 mg glyburide USP with 250 mg metformin hydrochloride USP, 2.5 mg glyburide USP with 500 mg metformin hydrochloride USP, and 5 mg glyburide USP with 500 mg metformin hydrochloride USP. In addition, each film-coated tablet contains the following inactive ingredients: microcrystalline cellulose, croscarmellose sodium, povidone, magnesium stearate, hypromellose, propylene glycol, polysorbate 80, talc, titanium dioxide and FD&C Yellow#6 aluminum lake. The 1.25 mg/250 mg and 5 mg/500 mg strengths also contain D&C Yellow#10 aluminum lake; The 2.5 mg/500 mg strength also contains FD&C Red#40 aluminum lake.
Meets USP Dissolution Test 2

12 CLINICAL PHARMACOLOGY

12.1 Mechanism of Action

Glyburide primarily lowers blood glucose by stimulating the release of insulin from the pancreas, an effect dependent upon functioning beta cells in the pancreatic islets. Sulfonylureas bind to the sulfonylurea receptor in the pancreatic beta-cell plasma membrane, leading to closure of the ATP-sensitive potassium channel, thereby stimulating the release of insulin.

Metformin is an antihyperglycemic agent that improves glucose tolerance in patients with type 2 diabetes, lowering both basal and postprandial plasma glucose. Metformin decreases hepatic glucose production, decreases intestinal absorption of glucose, and improves insulin sensitivity by increasing peripheral glucose uptake and utilization. With metformin therapy, insulin secretion remains unchanged while fasting insulin levels and daylong plasma insulin response may decrease.

12.3 Pharmacokinetics

Absorption

Glyburide and Metformin Hydrochloride

In bioavailability studies of glyburide and metformin hydrochloride 2.5 mg/500 mg and 5 mg/500 mg, the mean area under the plasma concentration versus time curve (AUC) for the glyburide component was 18% and 7%, respectively, greater than that of standard particle-size glyburide coadministered with metformin. The pharmacokinetics of metformin HCl component of glyburide and metformin hydrochloride was consistent with that of metformin HCl coadministered with glyburide.

Effect of food: Following administration of a single glyburide and metformin hydrochloride 5 mg/500 mg tablet with either a 20% glucose solution or a 20% glucose solution with food, there was no effect of food on the Cmax and a relatively small effect of food on the AUC of the glyburide component. The Tmax for the glyburide component was shortened from 7.5 hours to 2.75 hours with food compared to the same tablet strength administered fasting with a 20% glucose solution. The effect of food on the pharmacokinetics of the metformin component of glyburide and metformin hydrochloride was indeterminate. However, food is known to decrease the extent of and slightly delay the absorption of metformin, as shown by approximately a 40% lower mean peak plasma concentration (Cmax), a 25% lower area under the plasma concentration versus time curve (AUC), and a 35-minute prolongation of time to peak plasma concentration (Tmax) following administration of a single 850 mg tablet of metformin with food, compared to the same tablet strength administered fasting. The clinical relevance of these decreases is unknown.

Glyburide

Single-dose studies with standard particle-size glyburide tablets in normal subjects demonstrate significant absorption of glyburide within 1 hour, peak drug levels at about 4 hours, and low but detectable levels at 24 hours. Mean serum levels of glyburide, as reflected by areas under the serum concentration-time curve, increase in proportion to corresponding increases in dose. Bioequivalence has not been established between glyburide and metformin hydrochloride and single-ingredient standard particle-size glyburide products.

Metformin

The absolute bioavailability of a 500 mg metformin tablet given under fasting conditions is approximately 50% to 60%. Studies using single oral doses of metformin tablets of 500 mg and 1500 mg, and 850 mg to 2550 mg, indicate that there is a lack of dose proportionality with increasing doses, which is due to decreased absorption rather than an alteration in elimination. At usual clinical doses and dosing schedules of metformin, steady-state plasma concentrations of metformin are reached within 24 to 48 hours and are generally <1 mcg/mL.

Distribution

Glyburide

Sulfonylurea drugs are extensively bound to serum proteins. Displacement from protein binding sites by other drugs may lead to enhanced hypoglycemic action. In vitro, the protein binding exhibited by glyburide is predominantly non-ionic, whereas that of other sulfonylureas (chlorpropamide, tolbutamide, tolazamide) is predominantly ionic. Acidic drugs, such as phenylbutazone, warfarin, and salicylates, displace the ionic-binding sulfonylureas from serum proteins to a far greater extent than the non-ionic binding glyburide. It has not been shown that this difference in protein binding results in fewer drug-drug interactions with glyburide tablets in clinical use.

Metformin

The apparent volume of distribution (V/F) of metformin following single oral doses of 850 mg averaged 654±358 L. Metformin is negligibly bound to plasma proteins. Metformin partitions into erythrocytes, most likely as a function of time.

Metabolism and Elimination

Glyburide

The decrease of glyburide in the serum of normal healthy individuals is biphasic; the terminal half-life is about 10 hours. The major metabolite of glyburide is the 4-trans-hydroxy derivative.

A second metabolite, the 3-cis-hydroxy derivative, also occurs. These metabolites probably contribute no significant hypoglycemic action in humans since they are only weakly active (1/400 and 1/40 as active, respectively, as glyburide) in rabbits. Glyburide is excreted as metabolites in the bile and urine, approximately 50% by each route. This dual excretory pathway is qualitatively different from that of other sulfonylureas, which are excreted primarily in the urine.

Metformin

Intravenous single-dose studies in normal subjects demonstrate that metformin is excreted unchanged in the urine and does not undergo hepatic metabolism (no metabolites have been identified in humans) nor biliary excretion. Renal clearance (see Table 4) is approximately 3.5 times greater than creatinine clearance, which indicates that tubular secretion is the major route of metformin elimination. Following oral administration, approximately 90% of the absorbed drug is eliminated via the renal route within the first 24 hours, with a plasma elimination half-life of approximately 6.2 hours. In blood, the elimination half-life is approximately 17.6 hours, suggesting that the erythrocyte mass may be a compartment of distribution.

Specific Populations

Hepatic Impairment

No pharmacokinetic studies have been conducted in patients with hepatic insufficiency for either glyburide or metformin [see Warnings and Precautions (8.7)].

Renal Impairment

No information is available on the pharmacokinetics of glyburide in patients with renal insufficiency.

In patients with decreased renal function the plasma and blood half-life of metformin is prolonged and the renal clearance is decreased (Table 4); [see Dosage and Administration (2), Contraindications (4), and Warnings and Precautions (5.1)].

Geriatrics

There is no information on the pharmacokinetics of glyburide in elderly patients.

Limited data from controlled pharmacokinetic studies of metformin in healthy elderly subjects suggest that total plasma clearance is decreased, the half-life is prolonged, and Cmax is increased, when compared to healthy young subjects. From these data, it appears that the change in metformin pharmacokinetics with aging is primarily accounted for by a change in renal function (Table4); [see Dosage and Administration (2.3) and Warnings and Precautions (5.1)].

Table 4: Select Mean (±SD) Metformin Pharmacokinetic Parameters Following Single or Multiple Oral Doses of Metformin HCl

Subject Groups: Metformin HCl Dosea (number of subjects) | Cmaxb (mcg/mL) | Tmaxc (hrs) | Renal Clearance (mL/min)
Healthy, nondiabetic adults: 500 mg SDd (24) 850 mg SD (74)e 850 mg t.i.d. for 19 dosesf (9) | 1.03 (±0.33) 1.60 (±0.38) 2.01 (±0.42) | 2.75 (±0.81) 2.64 (±0.82) 1.79 (±0.94) | 600 (±132) 552 (±139) 642 (±173)
Adults with type 2 diabetes: 850 mg SD (23) 850 mg t.i.d. for 19 dosesf (9) | 1.48 (±0.5) 1.90 (±0.62) | 3.32 (±1.08) 2.01 (±1.22) | 491 (±138) 550 (±160)
Elderlyg, healthy nondiabetic adults: 850 mg SD (12) | 2.45 (±0.70) | 2.71 (±1.05) | 412 (±98)
Renal-impaired adults: 850 mg SD Mild (CLcrh 61 to 90 mL/min) (5) Moderate (CLcr 31 to 60 mL/min) (4) Severe (CLcr 10 to 30 mL/min) (6) | 1.86 (±0.52) 4.12 (±1.83) 3.93 (±0.92) | 3.20 (±0.45) 3.75 (±0.50) 4.01 (±1.10) | 384 (±122) 108 (±57) 130 (±90)
a All doses given fasting except the first 18 doses of the multiple-dose studies
b Peak plasma concentration
c Time to peak plasma concentration
d SD=single dose
e Combined results (average means) of 5 studies: mean age 32 years (range 23 to 59 years)
f Kinetic study done following dose 19, given fasting
g Elderly subjects, mean age 71 years (range 65 to 81 years)
h CLcr=creatinine clearance normalized to body surface area of 1.73 m^2

Gender

There is no information on the effect of gender on the pharmacokinetics of glyburide.

Metformin pharmacokinetic parameters did not differ significantly in subjects with or without type 2 diabetes when analyzed according to gender (males=19, females=16).

Race

No information is available on race differences in the pharmacokinetics of glyburide.

No studies of metformin pharmacokinetic parameters according to race have been performed.

13 NONCLINICAL TOXICOLOGY

13.1 Carcinogenesis, Mutagenesis, Impairment of Fertility

No animal studies have been conducted with the combined products in glyburide and metformin hydrochloride. The following data are based on findings in studies performed with the individual products.

Glyburide

Studies in rats with glyburide alone at doses up to 300 mg/kg/day (approximately 145 times the maximum recommended human daily dose of 20 mg for the glyburide component of glyburide and metformin hydrochloride based on body surface area comparisons) for 18 months revealed no carcinogenic effects. In a 2-year oncogenicity study of glyburide in mice, there was no evidence of treatment-related tumors.

There was no evidence of mutagenic potential of glyburide alone in the following in vitro tests: Salmonella microsome test (Ames test) and in the DNA damage/alkaline elution assay.

No evidence of impaired fertility was observed when doses up to 500 times the maximum recommended human dose of 20 mg of glyburide, based on body surface area comparisons, were administered to rats in reproduction studies.
Metformin

Long-term carcinogenicity studies have been performed in rats (dosing duration of 104 weeks) and mice (dosing duration of 91 weeks) at doses up to and including 900 mg/kg/day and 1500 mg/kg/day, respectively. These doses are both approximately 4 times the maximum recommendation human daily dose of 2000 mg on body surface area comparisons. No evidence of carcinogenicity with metformin was found in either male or female mice. Similarly, there was no tumorigenic potential observed with metformin in male rats. There was, however, an increased incidence of benign stromal uterine polyps in female rats treated with 900 mg/kg/day.

There was no evidence of a mutagenic potential of metformin in the following in vitro tests: Ames test (S. typhimurium), gene mutation test (mouse lymphoma cells), or chromosomal aberrations test (human lymphocytes). Results in the in vivo mouse micronucleus test were also negative.

Fertility of male or female rats was unaffected by metformin when administered at doses as high as 600 mg/kg/day, which is approximately 3 times the maximum recommended human daily dose of 2000 mg based on body surface area comparisons.

14 CLINICAL STUDIES

Patients with Inadequate Glycemic Control on Diet and Exercise Alone

In a 20-week, double-blind, placebo-controlled, multicenter U.S. clinical study, involving 806 drug-naive patients with type 2 diabetes, whose hyperglycemia was not adequately controlled with dietary management alone (baseline fasting plasma glucose [FPG] below 240 mg/dL, baseline hemoglobin A1c [HbA1c] between 7% and 11%), were randomized to receive initial therapy with placebo, 2.5 mg glyburide, 500 mg metformin HCl, glyburide and metformin hydrochloride 1.25 mg/250 mg, or glyburide and metformin hydrochloride 2.5 mg/500 mg. After 4 weeks, the dose was progressively increased to a maximum of 4 tablets daily as needed to reach a target FPG of 126 mg/dL. Study data at 20 weeks are summarized in Table 5.

Table 5: Mean Change in Hemoglobin A1c and Fasting Plasma Glucose in Patients Receiving Placebo, Glyburide, Metformin HCl or Glyburide and Metformin Hydrochloride at 20 Weeks
 | Placebo | Glyburide 2.5 mg tablets | Metformin HCl 500 mg tablets | Glyburide and Metformin Hydrochloride 1.25 mg/250 mg tablets | Glyburide and Metformin Hydrochloride 2.5 mg/500 mg tablets
Mean Final Dose | 0 mg | 5.3 mg | 1317 mg | 2.78 mg/557 mg | 4.1 mg/824 mg
Hemoglobin A1c | N=147 | N=142 | N=141 | N=149 | N=152
Baseline Mean (%) | 8.14 | 8.14 | 8.23 | 8.22 | 8.20
Mean Change from Baseline | −0.21 | −1.24 | −1.03 | −1.48 | −1.53
Difference from Placebo |  | −1.02 | −0.82 | −1.26a | −1.31a
Difference from Glyburide |  |  |  | −0.24b | −0.29b
Difference from Metformin |  |  |  | −0.44b | −0.49b
Fasting Plasma Glucose | N=159 | N=158 | N=156 | N=153 | N=154
Baseline Mean FPG (mg/dL) | 177.2 | 178.9 | 175.1 | 178 | 176.6
Mean Change from Baseline | 4.6 | −35.7 | −21.2 | −41.5 | −40.1
Difference from Placebo |  | −40.3 | −25.8 | −46.1a | −44.7a
Difference from Glyburide |  |  |  | −5.8c | −4.5c
Difference from Metformin |  |  |  | −20.3c | −18.9c
Final HbA1c Distribution (%) | N=147 | N=142 | N=141 | N=149 | N=152
<7% | 19.7% | 59.9% | 50.4% | 66.4% | 71.7%
≥7% and <8% | 37.4% | 26.1% | 29.8% | 25.5% | 19.1%
≥8% | 42.9% | 14.1% | 19.9% | 8.1% | 9.2%
a p<0.001
b p<0.05
c p=NS

Mean baseline body weight was 87 kg, 87 kg, 89 kg, 89 kg and 87 kg in the placebo, glyburide 2.5mg, metformin 500mg, glyburide and metformin hydrochloride 1.25mg/250mg and 2.5mg/500mg arms, respectively. Mean change in body weight from baseline to week 20 was -0.7 kg, +1.7 kg, -0.6 kg, +1.4 kg and +1.9 in the placebo, glyburide, metformin, glyburide and metformin hydrochloride 1.25mg/250mg and 2.5mg/500mg arms, respectively.

Patients with Inadequate Glycemic Control on Sulfonylurea Alone

In a 16-week, double-blind, active-controlled U.S. clinical study, a total of 639 patients with type 2 diabetes not adequately controlled (mean baseline HbA1c 9.5%, mean baseline FPG 213 mg/dL) while being treated with at least one-half the maximum dose of a sulfonylurea (e.g., glyburide 10 mg, glipizide 20 mg) were randomized to receive glyburide (fixed dose, 20 mg), metformin HCl (500 mg), glyburide and metformin hydrochloride 2.5 mg/500 mg, or glyburide and metformin hydrochloride 5 mg/500 mg. The doses of metformin HCl and glyburide and metformin hydrochloride were titrated to a maximum of 4 tablets daily as needed to achieve FPG <140 mg/dL. Study data at 16 weeks are summarized in Table 6.

Table 6: Mean Change in Hemoglobin A1c and Fasting Plasma Glucose in Patients Receiving Glyburide, Metformin HCl or Glyburide and Metformin Hydrochloride at 16 Weeks
 | Glyburide 5 mg tablets | Metformin HCl 500 mg tablets | Glyburide and Metformin Hydrochloride 2.5 mg/500 mg tablets | Glyburide and Metformin Hydrochloride 5 mg/500 mg tablets
Mean Final Dose | 20 mg | 1840 mg | 8.8 mg/1760 mg | 17 mg/1740 mg
Hemoglobin A1c | N=158 | N=142 | N=154 | N=159
Baseline Mean (%) | 9.63 | 9.51 | 9.43 | 9.44
Final Mean | 9.61 | 9.82 | 7.92 | 7.91
Difference from Glyburide |  |  | −1.69a | −1.70a
Difference from Metformin |  |  | −1.90a | −1.91a
Fasting Plasma Glucose | N=163 | N=152 | N=160 | N=160
Baseline Mean (mg/dL) | 218.4 | 213.4 | 212.2 | 210.2
Final Mean | 221.0 | 233.8 | 169.6 | 161.1
Difference from Glyburide |  |  | −51.3a | −59.9a
Difference from Metformin |  |  | −64.2a | −72.7a
Final HbA1c Distribution (%) | N=158 | N=142 | N=154 | N=159
<7% | 2.5% | 2.8% | 24.7% | 22.6%
≥7% and <8% | 9.5% | 11.3% | 33.1% | 37.1%
≥8% | 88% | 85.9% | 42.2% | 40.3%
a p<0.001

Weight gain due to glyburide was comparable in all three exposed groups.

16 HOW SUPPLIED/STORAGE AND HANDLING

Product: 50090-2030

NDC: 50090-2030-0 60 TABLET, FILM COATED in a BOTTLE

NDC: 50090-2030-2 100 TABLET, FILM COATED in a BOTTLE

NDC: 50090-2030-3 90 TABLET, FILM COATED in a BOTTLE

NDC: 50090-2030-4 180 TABLET, FILM COATED in a BOTTLE

Product: 50090-2031

NDC: 50090-2031-0 60 TABLET, FILM COATED in a BOTTLE

NDC: 50090-2031-2 180 TABLET, FILM COATED in a BOTTLE

17 PATIENT COUNSELING INFORMATION

Advise the patient to read the FDA-approved patient labeling (Patient Information).

Lactic Acidosis:

Explain the risks of lactic acidosis, its symptoms, and conditions that predispose to its development. Advise patients to discontinue glyburide and metformin hydrochloride immediately and to promptly notify their healthcare provider practitioner if unexplained hyperventilation, myalgia, malaise, unusual somnolence, or other nonspecific symptoms occur. Counsel patients against excessive alcohol intake and inform patients about importance of regular testing of renal function while receiving glyburide and metformin hydrochloride. Instruct patients to inform their doctor that they are taking glyburide and metformin hydrochloride prior to any surgical or radiological procedure, as temporary discontinuation may be required [see Warnings and Precautions (5.1)].

Hypoglycemia:

Inform patients that hypoglycemia may occur when taking glyburide and metformin hydrochloride. Explain to patients the risks of hypoglycemia, its symptoms and treatment, and conditions that predispose to its development [see Warnings and Precautions (5.2)].

Cardiovascular Mortality:

Inform patients that the administration of oral hypoglycemic drugs has been reported to be associated with increased cardiovascular mortality as compared to treatment with diet alone or diet plus insulin. Inform patients of the potential risks and benefits of glyburide and of alternative modes of therapy [see Warnings and Precautions (5.3)].

Vitamin B12 Deficiency:

Inform patients about importance of regular hematological testing while receiving glyburide and metformin hydrochloride [see Warnings and Precautions (5.5)].

Females of Reproductive Age:

Inform females that treatment with glyburide and metformin hydrochloride may result in ovulation in some premenopausal anovulatory women which may lead to unintended pregnancy [see Use in Specific Populations (8.3)].

Distributed by:
Rising Health, LLC
Saddle Brook, NJ 07663
Made in India
Code: TS/DRUGS/19/1993
Trademarks are the property of their respective owners.
Revised: 02/2019

PATIENT INFORMATION

Glyburide and Metformin Hydrochloride Tablets USP, for oral use

(glye’ bure ide and met for’ min hye” droe klor’ ide)

What is the most important information I should know about glyburide and metformin hydrochloride tablets?

Glyburide and metformin hydrochloride tablets can cause serious side effects, including:

Lactic Acidosis. Metformin hydrochloride, a medicine in glyburide and metformin hydrochloride tablets, can cause a rare, but serious, side effect called lactic acidosis (a build-up of lactic acid in the blood) that can cause death. Lactic acidosis is a medical emergency and must be treated in a hospital.

Stop taking glyburide and metformin hydrochloride tablets and call your healthcare provider right away if you get any of the following symptoms of lactic acidosis:

- feel very weak and tired
- have unusual sleepiness or sleep longer than usual
- have unusual (not normal) muscle pain
- feel cold, especially in your arms and legs
- have trouble breathing
- feel dizzy or lightheaded
- have unexplained stomach or intestinal problems with nausea and vomiting, or diarrhea
- have a slow or irregular heartbeat

You have a higher chance of getting lactic acidosis if you:

- have severe kidney problems. “See “Do not take glyburide and metformin hydrochloride tablets if you:”
- have liver problems.
- drink a lot of alcohol (very often or short-term “binge” drinking).
- get dehydrated (lose a large amount of body fluids). This can happen if you are sick with a fever, vomiting, or diarrhea. Dehydration can also happen when you sweat a lot with activity or exercise and do not drink enough fluids.
- have certain x-ray tests with injectable dyes or contrast agents.
- have surgery or other procedures for which you need to restrict the amount of food and liquid you eat and drink.
- have congestive heart failure.
- have a heart attack, severe infection, or stroke.
- are 65 years of age or older.

Tell your healthcare provider if you have any of the problems in the list above.

Tell your healthcare provider that you are taking glyburide and metformin hydrochloride tablets before you have surgery or x-ray tests.

Your healthcare provider may need to stop glyburide and metformin hydrochloride tablets for a while if you have surgery or certain x-ray tests.

Glyburide and metformin hydrochloride tablets can have other serious side effects. See “What are the possible side effects of glyburide and metformin hydrochloride tablets?”

What is glyburide and metformin hydrochloride tablets?

- Glyburide and metformin hydrochloride tablets are a prescription medicine that contains glyburide (sulfonylurea) and metformin hydrochloride. Glyburide and metformin hydrochloride tablets is used with diet and exercise to help control high blood sugar (hyperglycemia) in adults with type 2 diabetes.
- It is not known if glyburide and metformin hydrochloride tablets are safe and effective in children under 18 years of age.

Do not take glyburide and metformin hydrochloride tablets if you:

- have severe kidney problems.
- are allergic to metformin hydrochloride, glyburide or any of the ingredients in glyburide and metformin hydrochloride tablets. See the end of this Patient Information leaflet for a complete list of ingredients in glyburide and metformin hydrochloride tablets.
- have a condition called metabolic acidosis, including diabetic ketoacidosis (high levels of certain acids called “ketones” in your blood or urine).
- take bosentan.

Before taking glyburide and metformin hydrochloride tablets tell your healthcare provider about all medical conditions, including if you:

- have a history or risk for diabetic ketoacidosis. See “Do not take glyburide and metformin hydrochloride tablets if you:”
- have kidney problems.
- have liver problems.
- have heart problems, including congestive heart failure.
- are 65 year of age or older.
- drink alcohol very often, or drink a lot of alcohol in short-term “binge” drinking.
- have or any members of your family have glucose-6-phosphate dehydrogenase (G6PD) deficiency.
- are taking insulin or another sulfonylurea medicine.
- are pregnant or plan to become pregnant. It is not known if glyburide and metformin hydrochloride tablets will harm your unborn baby. You should not take glyburide and metformin hydrochloride tablets during the last 2 weeks of your pregnancy. If you are pregnant, talk with your healthcare provider about the best way to control your blood sugar while you are pregnant.
- are a woman who has not gone through menopause (premenopausal) who does not have periods regularly or at all. Glyburide and metformin hydrochloride tablets can cause the release of an egg from an ovary in a woman (ovulation). This can increase your chance of getting pregnant.
- are breastfeeding or plan to breastfeed. It is not known if glyburide one of the medicines in glyburide and metformin hydrochloride tablets passes into your breast milk. Metformin the other medicine in glyburide and metformin hydrochloride tablets can pass into your breastmilk. Talk with your healthcare provider about the best way to feed your baby while you take glyburide and metformin hydrochloride tablets.

Tell your healthcare provider about all the medicines you take, including prescription and over-the-counter medicines, vitamins, and herbal supplements. Know the medicines you take. Keep a list of them to show your healthcare provider and pharmacist when you get a new medicine.

Glyburide and metformin hydrochloride tablets may affect the way other medicines work, and other medicines may affect how glyburide and metformin hydrochloride tablet works.

How should I take glyburide and metformin hydrochloride tablets?

- Take glyburide and metformin hydrochloride tablets exactly as your healthcare provider tells you.
- glyburide and metformin hydrochloride tablets should be taken 2 times each day with meals to help decrease an upset stomach side effect and avoid hypoglycemia.
- If you are taking colesevelam and glyburide and metformin hydrochloride tablets, take your glyburide and metformin hydrochloride tablets at least 4 hours before taking your colesevelam.
- Your healthcare provider should do blood tests to check how well your kidneys are working before and during your treatment with glyburide and metformin hydrochloride tablets.
- Your healthcare provider will check your diabetes with regular blood tests, including your blood sugar levels and your hemoglobin A1c.
- Low blood sugar (hypoglycemia) can happen more often when glyburide and metformin hydrochloride tablets is taken with certain other diabetes medicines. Talk to your healthcare provider about how to prevent, recognize, and manage low blood sugar. See “What are the possible side effects of glyburide and metformin hydrochloride tablets?”
- Check your blood sugar as your healthcare provider tells you to.
- If you take too much glyburide and metformin hydrochloride, call your healthcare provider or go to the nearest hospital emergency room right away.

What should I avoid while taking glyburide and metformin hydrochloride tablets?

- Do not drink a lot of alcoholic drinks while taking glyburide and metformin hydrochloride tablets. This means you should not binge drink for short periods, and you should not drink a lot of alcohol on a regular basis. Alcohol can increase the chance of getting lactic acidosis.
- Do not drive, operate machinery, or do other dangerous activities until you know how glyburide and metformin hydrochloride tablets affects you.

What are the possible side effects of glyburide and metformin hydrochloride tablets?

Glyburide and metformin hydrochloride tablets can cause serious side effects, including:

- See “What is the most important information I should know about glyburide and metformin hydrochloride tablets?”
- low blood sugar (hypoglycemia). Low blood sugar is a serious, but common side effect of glyburide and metformin hydrochloride tablets. If you take glyburide and metformin hydrochloride tablets with another medicine that can cause low blood sugar, such as insulin, you have a higher risk of getting low blood sugar. The dose of insulin or other diabetic medicines may need to be lowered while you take glyburide and metformin hydrochloride tablets. Signs and symptoms of low blood sugar may include:
  - headache
  - hunger
  - dizziness
  - drowsiness
  - fast heartbeat
  - sweating
  - weakness
  - confusion
  - blurred vision
  - irritability
  - shaking or feeling jittery
  - anxiety
  - slurred speech
  - mood changes
- increased risk of cardiovascular deaths. Taking oral hypoglycemic medicines like glyburide and metformin hydrochloride tablets to treat diabetes have increased the risk of death from heart disease or stroke compared to treating diabetes with diet alone or diet and insulin.
- hemolytic anemia. People with G6PD deficiency who take glyburide and metformin hydrochloride tablets may develop hemolytic anemia (fast breakdown of red blood cells).
- low vitamin B12 (vitamin B12 deficiency). Using glyburide and metformin hydrochloride tablets may cause a decrease in the amount of vitamin B12 in your blood, especially if you have had low vitamin B12 levels before. Your healthcare provider may do blood tests to check your vitamin B12 levels.

The most common side effects of glyburide and metformin hydrochloride tablets include:

- diarrhea
- vomiting
- headache
- stomach pain
- nausea
- dizziness

These are not all the possible side effects of glyburide and metformin hydrochloride tablets.

Call your doctor for medical advice about side effects. You may report side effects to FDA at 1-800-FDA-1088.

How should I store glyburide and metformin hydrochloride tablets?

- Store glyburide and metformin hydrochloride tablets at room temperature between 68°F to 77°F (20°C to 25°C).

Keep glyburide and metformin hydrochloride tablets and all medicines out of the reach of children.

General information about the safe and effective use glyburide and metformin hydrochloride tablets.

Medicines are sometimes prescribed for purposes other than those listed in a Patient Information leaflet. Do not use glyburide and metformin hydrochloride tablets for a condition for which it was not prescribed. Do not give glyburide and metformin hydrochloride tablets to other people, even if they have the same symptoms you have. It may harm them.

You can ask your pharmacist or healthcare provider for information about glyburide and metformin hydrochloride tablets that is written for health professionals.

What are the ingredients in glyburide and metformin hydrochloride tablets?

Active ingredients: glyburide and metformin hydrochloride.

Inactive ingredients: microcrystalline cellulose, croscarmellose sodium, povidone, magnesium stearate, hypromellose, propylene glycol, polysorbate 80, talc, titanium dioxide and FD&C Yellow#6 aluminum lake. The 1.25 mg/250 mg and 5 mg/500 mg strengths also contain D&C Yellow#10 aluminum lake; The 2.5 mg/500 mg strength also contains FD&C Red#40 aluminum lake.

For more information, call Rising Health, LLC at 1-833-395-6928.

Trademarks are the property of their respective owners.

Distributed by:
Rising Health, LLC
Saddle Brook, NJ 07663
Made in India
Code: TS/DRUGS/19/1993
This Patient Package Insert has been approved by the U.S. Food and Drug Administration
Revised: 02/2019